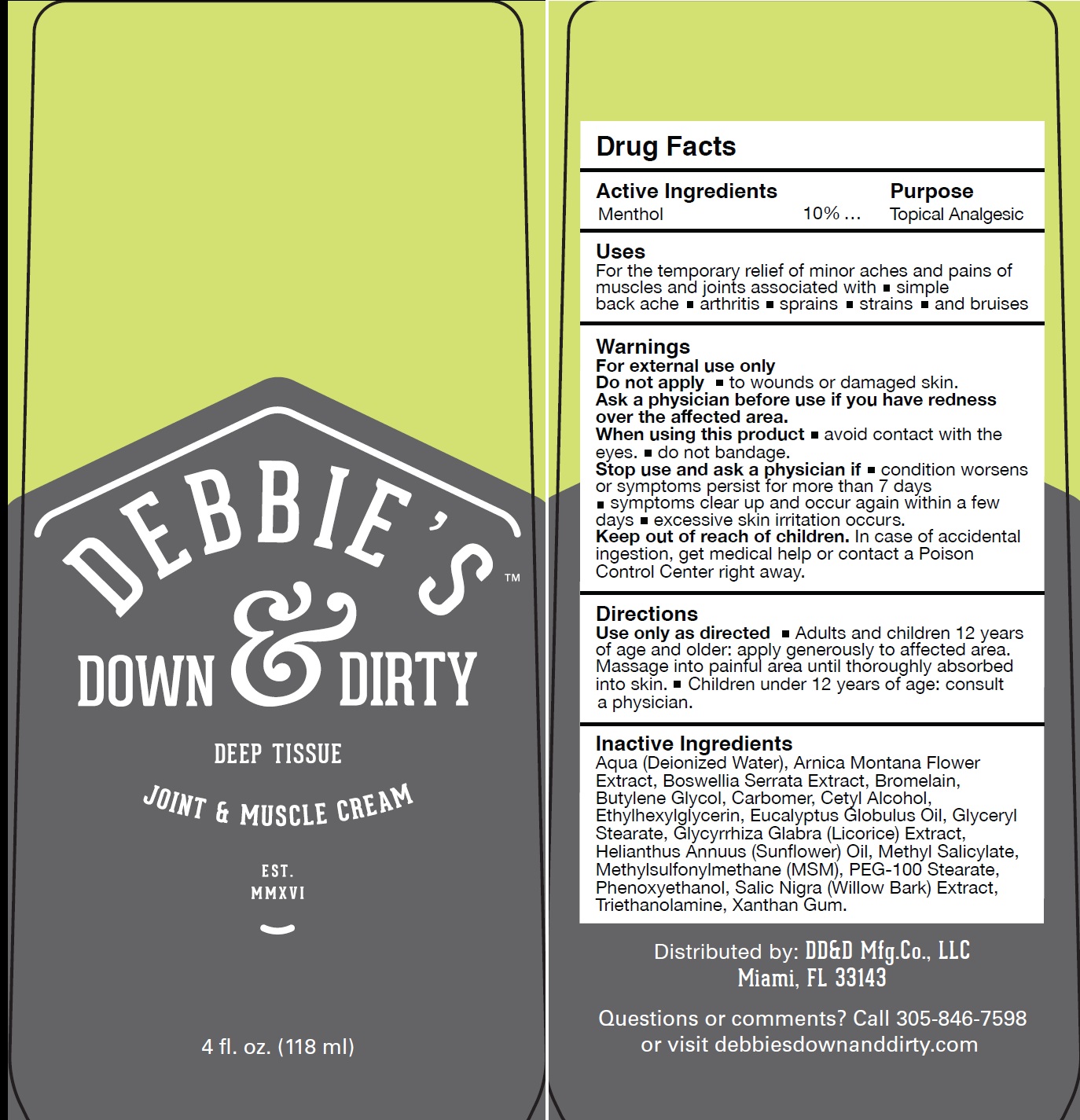 DRUG LABEL: Debbies Down and Dirty Deep Tissue Joint and Muscle
NDC: 71523-833 | Form: CREAM
Manufacturer: DD&D Manufacturing Co., Ltd
Category: otc | Type: HUMAN OTC DRUG LABEL
Date: 20231111

ACTIVE INGREDIENTS: MENTHOL 100 mg/1 mL
INACTIVE INGREDIENTS: HELIANTHUS ANNUUS FLOWERING TOP; METHYL SALICYLATE; DIMETHYL SULFONE; PEG-100 STEARATE; PHENOXYETHANOL; WILLOW BARK; TROLAMINE; XANTHAN GUM; WATER; ARNICA MONTANA FLOWER; INDIAN FRANKINCENSE; BROMELAINS; BUTYLENE GLYCOL; CARBOXYPOLYMETHYLENE; CETYL ALCOHOL; ETHYLHEXYLGLYCERIN; EUCALYPTUS OIL; GLYCERYL MONOSTEARATE; GLYCYRRHIZA GLABRA

Debbie's Down & Dirty Deep Tissue Joint and Muscle Cream

Active Ingredients

Menthol 10%

Purpose

Topical Analgesic

Uses

For the temporary relief of minor aches and pains of muscles and joints associated with simple back ache • arthritis • sprains • strains • and bruises

Warnings

For external use only

Do not apply

to wounds or damaged skin.

Ask a physician before use if

you have redness over the affected area.

When using this product

- avoid contact with the eyes.
- do not bandage.

Stop use and ask a physician if

- condition worsens or symptoms persist for more than 7 days
- symptoms clear up and occur again within a few days
- excessive skin irritation occurs.

Keep out of reach of children.

In case of accidental ingestion, get medical help or contact a Poison Control Center right away.

Directions

Use only as directed Adults and children 12 years of age and older: apply generously to affected area. Massage into painful area until thoroughly absorbed into skin. Children under 12 years of age: consult a physician.

Inactive Ingredients

Aqua (Deionized Water), Arnica Montana Flower Extract, Boswellia Serrata Extract, Bromelain, Butylene Glycol, Carbomer, Cetyl lcohol, Ethylhexylglycerin, Eucalyptus Globulus Oil, Glyceryl Stearate, Glycyrrhiza Glabra (Licorice) Extract, Helianthus Annuus (Sunflower) Oil, Methyl Salicylate, Methylsulfonylmethane (MSM), PEG-100 Stearate, Phenoxyethanol, Salic Nigra (Willow Bark) Extract, Triethanolamine, Xanthan Gum.